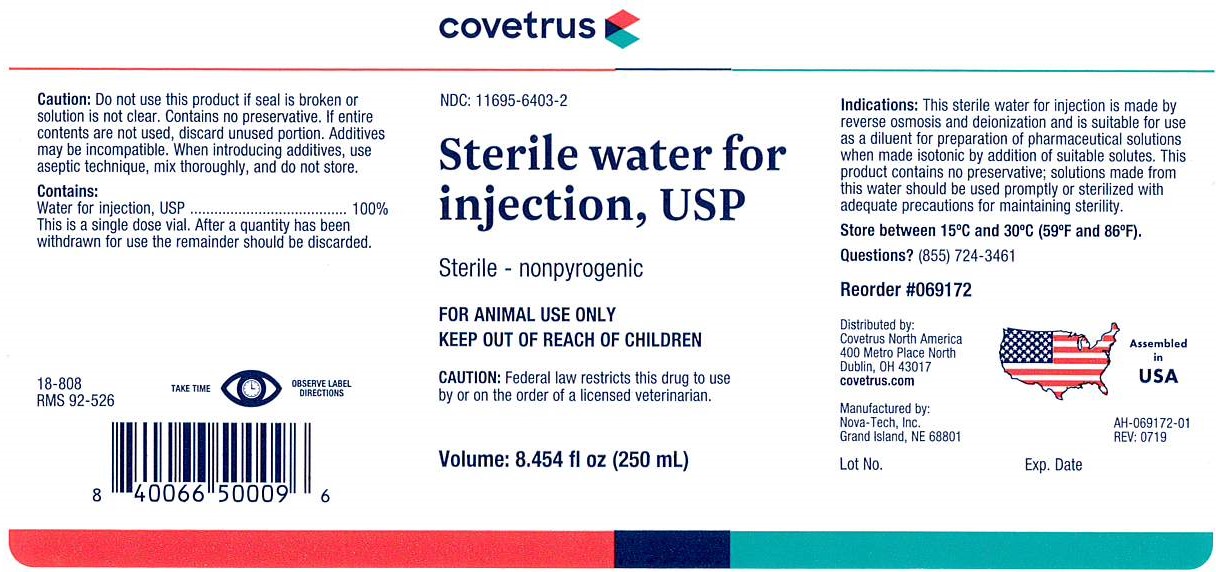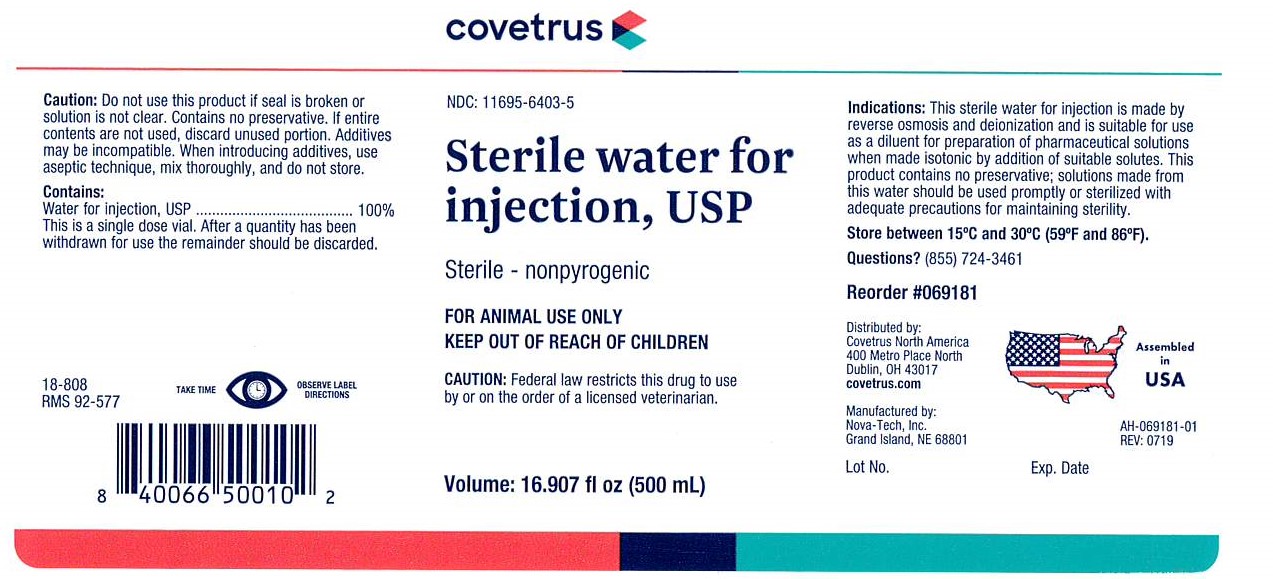 DRUG LABEL: Sterile Water
NDC: 11695-6403 | Form: INJECTION
Manufacturer: Covetrus
Category: animal | Type: PRESCRIPTION ANIMAL DRUG LABEL
Date: 20191202

ACTIVE INGREDIENTS: Water 500 mL/500 mL

Sterile Water For Injection

Caution:

Do not use this product if seal is broken or
solution is not clear. Contains no preservative. If entire
contents are not used, discard unused portion.
Additives may be incompatible. When introducing
additives, use aseptic technique, mix thoroughly, and
do not store.

Contains:

Water for Injection, USP .................................... 100%
This is a single dose vial. After a quantity has been withdrawn for use the remainder should be discarded.

GENERAL PRECAUTIONS

TAKE TIME OBSERVE LABEL DIRECTIONS

GENERAL PRECAUTIONS

FOR ANIMAL USE ONLY

KEEP OUT OF REACH OF CHILDREN

Caution:

Federal law restricts this drug to use
by or on the order of a licensed veterinarian.

Indications:

This sterile water for injection is made by
reverse osmosis and deionization and is suitable for
use as a diluent for preparation of pharmaceutical
solutions when made isotonic by addition of suitable
solutes. This product contains no preservative;
solutions made from this water should be used
promptly or sterilized with adequate precautions for
maintaining sterility.

STORAGE AND HANDLING

Store between 15 degrees C and 30 degrees C (59 degrees F and 86 degrees F).

INFORMATION FOR OWNERS/CAREGIVERS

18-808

RMS 92-526

NDC: 11695-6403-2

Sterile - nonpyrogenic

Volume: 8.454 fl oz (250 mL)

Questions? (855) 724-3461

Reorder #069172

Distributed by:
Covetrus North America

400 Metro Place North
Dublin, OH 43017

covetrus.com

Manufactured by
Nova-Tech, Inc.
Grand Island, NE 68801

Lot No.

Exp. Date

Assembled in USA

AH-069172-01

REV: 0719